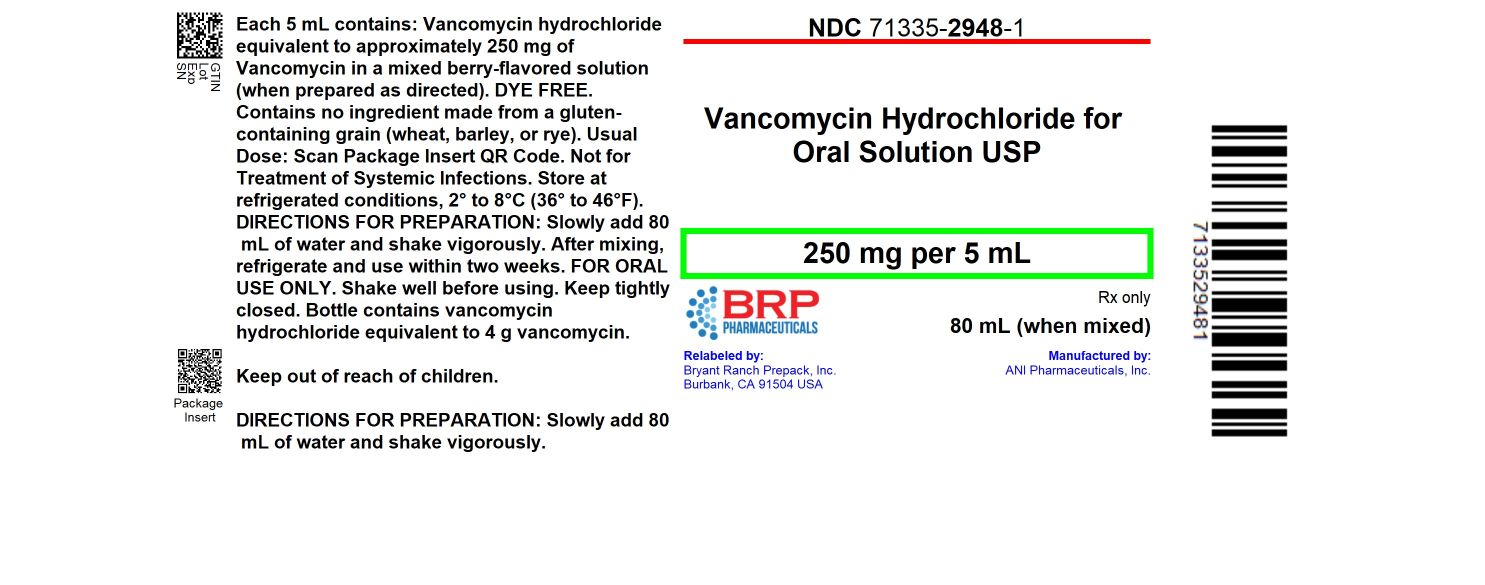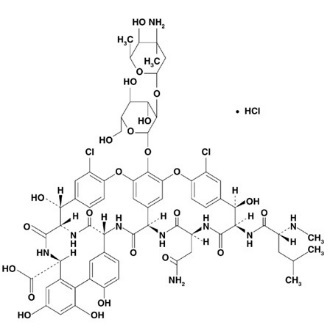 DRUG LABEL: Vancomycin Hydrochloride
NDC: 71335-2948 | Form: POWDER, FOR SOLUTION
Manufacturer: Bryant Ranch Prepack
Category: prescription | Type: HUMAN PRESCRIPTION DRUG LABEL
Date: 20251106

ACTIVE INGREDIENTS: VANCOMYCIN HYDROCHLORIDE 250 mg/5 mL
INACTIVE INGREDIENTS: ANHYDROUS CITRIC ACID; SODIUM BENZOATE; SUCRALOSE

Vancomycin Hydrochloride for Oral Solution USP
Rx only

To reduce the development of drug-resistant bacteria and maintain the effectiveness of Vancomycin Hydrochloride for Oral Solution and other antibacterial drugs, Vancomycin Hydrochloride for Oral Solution should be used only to treat or prevent infections that are proven or strongly suspected to be caused by bacteria.

This preparation for the treatment of colitis is for oral use only and is not systemically absorbed. Vancomycin Hydrochloride for Oral Solution must be given orally for treatment of staphylococcal enterocolitis and antibiotic-associated pseudomembranous colitis caused by Clostridium difficile. Orally administered Vancomycin Hydrochloride for Oral Solution is not effective for other types of infection.

Parenteral administration of vancomycin is not effective for treatment of staphylococcal enterocolitis and antibiotic-associated pseudomembranous colitis caused by C. difficile. If parenteral vancomycin therapy is desired, use an intravenous preparation of vancomycin and consult the package insert accompanying that preparation.

DESCRIPTION

Vancomycin Hydrochloride for Oral Solution USP contains chromatographically purified vancomycin hydrochloride USP, a tricyclic glycopeptide antibiotic derived from Amycolatopsis orientalis (formerly Nocardia orientalis), which has the chemical formula C66H75Cl2N9O24•HCl. The molecular weight of vancomycin hydrochloride is 1,485.73; 500 mg of the base is equivalent to 0.34 mmol.

Vancomycin hydrochloride has the following structural formula:

Vancomycin Hydrochloride for Oral Solution USP is intended for reconstitution with water. Each 5 mL of reconstituted solution contains vancomycin hydrochloride equivalent to 250 mg (0.17 mmol) vancomycin.

Inactive ingredients: citric acid anhydrous, sodium benzoate, sucralose, and mixed berry flavor. Contains no ingredient made from a gluten-containing grain (wheat, barley or rye).

CLINICAL PHARMACOLOGY

Vancomycin is poorly absorbed after oral administration. During multiple dosing of 250 mg every 8 hours for 7 doses, fecal concentrations of vancomycin in volunteers exceeded 100 mg/kg in the majority of samples. No blood concentrations were detected and urinary recovery did not exceed 0.76%. In anephric patients with no inflammatory bowel disease, blood concentrations of vancomycin were barely measurable (0.66 mcg/mL) in 2 of 5 subjects who received 2 g of Vancomycin Hydrochloride for Oral Solution daily for 16 days. No measurable blood concentrations were attained in the other 3 subjects. With doses of 2 g daily, very high concentrations of drug can be found in the feces (>3,100 mg/kg) and very low concentrations (<1 mcg/mL) can be found in the serum of patients with normal renal function who have pseudomembranous colitis. Orally administered vancomycin does not usually enter the systemic circulation even when inflammatory lesions are present. After multiple-dose oral administration of vancomycin, measurable serum concentrations may infrequently occur in patients with active C. difficile-induced pseudomembranous colitis, and, in the presence of renal impairment, the possibility of accumulation exists.

Microbiology

The bactericidal action of vancomycin results primarily from inhibition of cell-wall biosynthesis. In addition, vancomycin alters bacterial-cell-membrane permeability and RNA synthesis.

NOTE: The oral form of vancomycin is effective only for the infections noted in the INDICATIONS AND USAGE section. The oral form is not effective for any other type of infection.

Vancomycin has been shown to be active against most strains of the following microorganisms in clinical infections as described in the INDICATIONS AND USAGE section.

Aerobic gram-positive microorganisms
Staphylococcus aureus (including methicillin-resistant strains) associated with enterocolitis

Aerobic gram-positive microorganisms
Clostridium difficile antibiotic-associated pseudomembranous colitis

INDICATIONS AND USAGE

Vancomycin Hydrochloride for Oral Solution is administered orally for treatment of enterocolitis caused by Staphylococcus aureus (including methicillin-resistant strains) and antibiotic-associated pseudomembranous colitis caused by C. difficile. Parenteral administration of vancomycin is not effective for the above indications; therefore, Vancomycin Hydrochloride for Oral Solution must be given orally for these infections. Orally administered Vancomycin Hydrochloride for Oral Solution is not effective for other types of infection.

To reduce the development of drug-resistant bacteria and maintain the effectiveness of Vancomycin Hydrochloride for Oral Solution and other antibacterial drugs, Vancomycin Hydrochloride for Oral Solution should be used only to treat or prevent infections that are proven or strongly suspected to be caused by susceptible bacteria. When culture and susceptibility information are available, they should be considered in selecting or modifying antibacterial therapy. In the absence of such data, local epidemiology and susceptibility patterns may contribute to the empiric selection of therapy.

CONTRAINDICATIONS

Vancomycin Hydrochloride for Oral Solution is contraindicated in patients with known hypersensitivity to vancomycin.

WARNINGS

Nephrotoxicity

Nephrotoxicity (e.g., reports of renal failure, renal impairment, blood creatinine increased) has occurred following oral vancomycin hydrochloride therapy in randomized controlled clinical trials, and can occur either during or after completion of therapy. The risk of nephrotoxicity is increased in patients over 65 years of age.

In patients over 65 years of age, including those with normal renal function prior to treatment, renal function should be monitored during and following treatment with vancomycin oral solution to detect potential vancomycin induced nephrotoxicity.

Ototoxicity

Ototoxicity has occurred in patients receiving vancomycin. It may be transient or permanent. It has been reported mostly in patients who have been given excessive intravenous doses, who have an underlying hearing loss, or who are receiving concomitant therapy with another ototoxic agent, such as an aminoglycoside. Serial tests of auditory function may be helpful in order to minimize the risk of ototoxicity.

Severe dermatologic reactions such as toxic epidermal necrolysis (TEN), Stevens-Johnson syndrome (SJS), drug reaction with eosinophilia and systemic symptoms (DRESS), acute generalized exanthematous pustulosis (AGEP), and linear IgA bullous dermatosis (LABD) have been reported in association with the use of vancomycin. Cutaneous signs or symptoms reported include skin rashes, mucosal lesions, and blisters.

Discontinue Vancomycin Hydrochloride for Oral Solution at the first appearance of signs and symptoms of TEN, SJS, DRESS, AGEP, or LABD.

Clostridium Difficile Associated Diarrhea (CDAD)

Significant systemic absorption has been reported in some patients (e.g., patients with renal insufficiency and/or colitis) who have taken multiple oral doses of vancomycin hydrochloride for C. difficile-associated diarrhea. In these patients, serum vancomycin concentrations reached therapeutic levels for the treatment of systemic infections. Some patients with inflammatory disorders of the intestinal mucosa also may have significant systemic absorption of vancomycin. These patients may be at risk for the development of adverse reactions associated with higher doses of vancomycin oral solution; therefore, monitoring of serum concentrations of vancomycin may be appropriate in some instances, e.g., in patients with renal insufficiency and/or colitis or in those receiving concomitant therapy with an aminoglycoside antibacterial drug.

PRECAUTIONS

Use of vancomycin may result in the overgrowth of non-susceptible bacteria. If superinfection occurs during therapy, appropriate measures should be taken.

Prescribing vancomycin in the absence of a proven or strongly suspected bacterial infection is unlikely to provide benefit to the patient and increases the risk of the development of drug resistant bacteria.

Hemorrhagic occlusive retinal vasculitis, including permanent loss of vision, occurred in patients receiving intracameral or intravitreal administration of vancomycin during or after cataract surgery. The safety and efficacy of vancomycin administered by the intracameral or intravitreal route have not been established by adequate and well-controlled studies. Vancomycin is not indicated for prophylaxis of endophthalmitis.

Pregnancy

Animal reproduction studies have not been conducted with vancomycin. It is not known whether vancomycin can affect reproduction capacity. In a controlled clinical study, the potential ototoxic and nephrotoxic effects of vancomycin on infants were evaluated when the drug was administered intravenously to pregnant women for serious staphylococcal infections complicating intravenous drug abuse. Vancomycin was found in cord blood. No sensorineural hearing loss or nephrotoxicity attributable to vancomycin was noted. One infant whose mother received vancomycin in the third trimester experienced conductive hearing loss that was not attributed to the administration of vancomycin. Because the number of patients treated in this study was limited and vancomycin was administered only in the second and third trimesters, it is not known whether vancomycin causes fetal harm. Vancomycin Hydrochloride for Oral Solution should be given to a pregnant woman only if clearly needed.

Nursing Mothers

Vancomycin is excreted in human milk based on information obtained with the intravenous administration of vancomycin. However, systemic absorption of vancomycin is very low following oral administration of Vancomycin Hydrochloride for Oral Solution (see CLINICAL PHARMACOLOGY). It is not known whether oral vancomycin is excreted in human milk, as no studies of vancomycin concentration in human milk after oral administration have been done. Caution should be exercised when Vancomycin Hydrochloride for Oral Solution is administered to a nursing woman. Because of the potential for adverse events, a decision should be made whether to discontinue nursing or discontinue the drug, taking into account the importance of the drug to the mother.

Geriatric Use

In clinical trials, 54% of vancomycin hydrochloride-treated subjects were > 65 years of age. Of these, 40% were between the ages of > 65 and 75, and 60% were > 75 years of age.

Clinical studies with vancomycin hydrochloride in C. difficile-associated diarrhea have demonstrated that geriatric subjects are at increased risk of developing nephrotoxicity following treatment with oral vancomycin hydrochloride, which may occur during or after completion of therapy. In patients over 65 years of age, including those with normal renal function prior to treatment, renal function should be monitored during and following treatment with vancomycin hydrochloride to detect potential vancomycin induced nephrotoxicity.

Patients over 65 years of age may take longer to respond to therapy compared to patients 65 years of age and younger. Clinicians should be aware of the importance of appropriate duration of vancomycin hydrochloride treatment in patients over 65 years of age and not discontinue or switch to alternative treatment prematurely.

Information for Patients

Severe Dermatologic Reactions
Advise patients about the signs and symptoms of serious skin manifestations. Instruct patients to stop taking Vancocin immediately and promptly seek medical attention at the first signs or symptoms of skin rash, mucosal lesions and blisters (see WARNINGS).

Patients should be counseled that antibacterial drugs including Vancomycin Hydrochloride for Oral Solution should only be used to treat bacterial infections. They do not treat viral infections (e.g., the common cold). When Vancomycin Hydrochloride for Oral Solution is prescribed to treat a bacterial infection, patients should be told that although it is common to feel better early in the course of therapy, the medication should be taken exactly as directed. Skipping doses or not completing the full course of therapy may (1) decrease the effectiveness of the immediate treatment and (2) increase the likelihood that bacteria will develop resistance and will not be treatable by Vancomycin Hydrochloride for Oral Solution or other antibacterial drugs in the future.

ADVERSE REACTIONS

Nephrotoxicity

Nephrotoxicity (e.g., reports of renal failure, renal impairment, blood creatinine increased) occurred in 5% of subjects treated with vancomycin hydrochloride. Nephrotoxicity following vancomycin hydrochloride typically first occurred within one week after completion of treatment (median day of onset was Day 16). Nephrotoxicity following vancomycin hydrochloride occurred in 6% of subjects over 65 years of age and 3% of subjects 65 years of age and younger. Nephrotoxicity can also occur during oral vancomycin administration.

The incidences of hypokalemia, urinary tract infection, peripheral edema, insomnia, constipation, anemia, depression, vomiting, and hypotension were higher among subjects over 65 years of age than in subjects 65 years of age and younger.

Discontinuation of study drug due to adverse events occurred in 7% of subjects treated with vancomycin hydrochloride. The most common adverse events leading to discontinuation of vancomycin hydrochloride were C. difficile colitis (< 1%), nausea (< 1%), and vomiting (< 1%).

Ototoxicity

Cases of hearing loss associated with intravenously administered vancomycin have been reported. Most of these patients had kidney dysfunction or a preexisting hearing loss or were receiving concomitant treatment with an ototoxic drug. Vertigo, dizziness, and tinnitus have been reported rarely.

Hematopoietic

Reversible neutropenia, usually starting 1 week or more after onset of intravenous therapy with vancomycin or after a total dosage of more than 25 g, has been reported for several dozen patients. Neutropenia appears to be promptly reversible when vancomycin is discontinued. Thrombocytopenia has rarely been reported.

Miscellaneous

Patients have been reported to have had anaphylaxis, drug fever, nausea, chills, eosinophilia, rashes including exfoliative dermatitis, Stevens-Johnson syndrome (see WARNINGS, Severe Dermatologic Reactions), and vasculitis in association with the administration of vancomycin.

A condition has been reported that is similar to the IV-induced syndrome with symptoms consistent with anaphylactoid reactions, including hypotension, wheezing, dyspnea, urticaria, pruritus, flushing of the upper body (“Red Man Syndrome”), pain and muscle spasm of the chest and back. These reactions usually resolve within 20 minutes but may persist for several hours.

Post Marketing Reports

Skin and Subcutaneous Tissue Disorders
Severe dermatologic reactions such as toxic epidermal necrolysis (TEN), drug reaction with eosinophilia and systemic symptoms (DRESS), acute generalized exanthematous pustulosis (AGEP), and linear IgA bullous dermatosis (LABD) (see WARNINGS, Severe Dermatologic Reactions).

OVERDOSAGE

Supportive care is advised, with maintenance of glomerular filtration. Vancomycin is poorly removed by dialysis. Hemofiltration and hemoperfusion with polysulfone resin have been reported to result in increased vancomycin clearance.

For current information on the management of overdosage, contact the National Poison Control Center at 1-800-222-1222 or www.poison.org.

DOSAGE AND ADMINISTRATION

Adults

Vancomycin Hydrochloride for Oral Solution is used in treating antibiotic-associated pseudomembranous colitis caused by C. difficile and staphylococcal enterocolitis. Vancomycin Hydrochloride for Oral Solution is not effective by the oral route for other types of infections. The usual adult total daily dosage is 500 mg to 2 g administered orally in 3 or 4 divided doses for 7 to 10 days.

Pediatric Patients

The usual daily dosage is 40 mg/kg in 3 or 4 divided doses for 7 to 10 days. The total daily dosage should not exceed 2 g.

PREPARATION AND STABILITY

Mix the contents of the bottle with water as directed below. When reconstituted, each 5 mL contains approximately 250 mg of vancomycin. These mixtures may be kept for two weeks in a refrigerator without significant loss of potency.

Directions for mixing Vancomycin Hydrochloride for Oral Solution USP:

80 mL – Slowly add 80 mL water and shake vigorously.

150 mL – Slowly add 150 mL water and shake vigorously.

300 mL – Slowly add 300 mL water and shake vigorously.

The appropriate oral solution dose may be diluted in 1 oz of water and given to the patient to drink. The diluted material may be administered via nasogastric tube.

HOW SUPPLIED

Vancomycin Hydrochloride for Oral Solution USP equivalent to 250 mg per 5 mL vancomycin is available as:

NDC: 71335-2948-1: 80 mL (4 g) in a Bottle

Store at refrigerated conditions, 2° to 8°C (36° to 46°F).

After mixing, refrigerate and use within two weeks. Shake well before using. Keep tightly closed.

Repackaged/Relabeled by:
Bryant Ranch Prepack, Inc.

Burbank, CA 91504

PACKAGE LABEL

Vancomycin Hcl 250 mg/5ml Solution #80